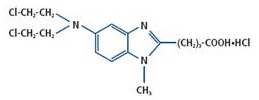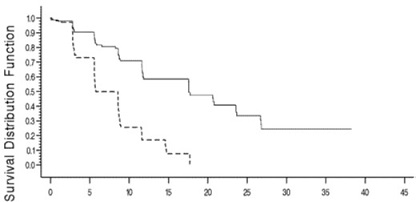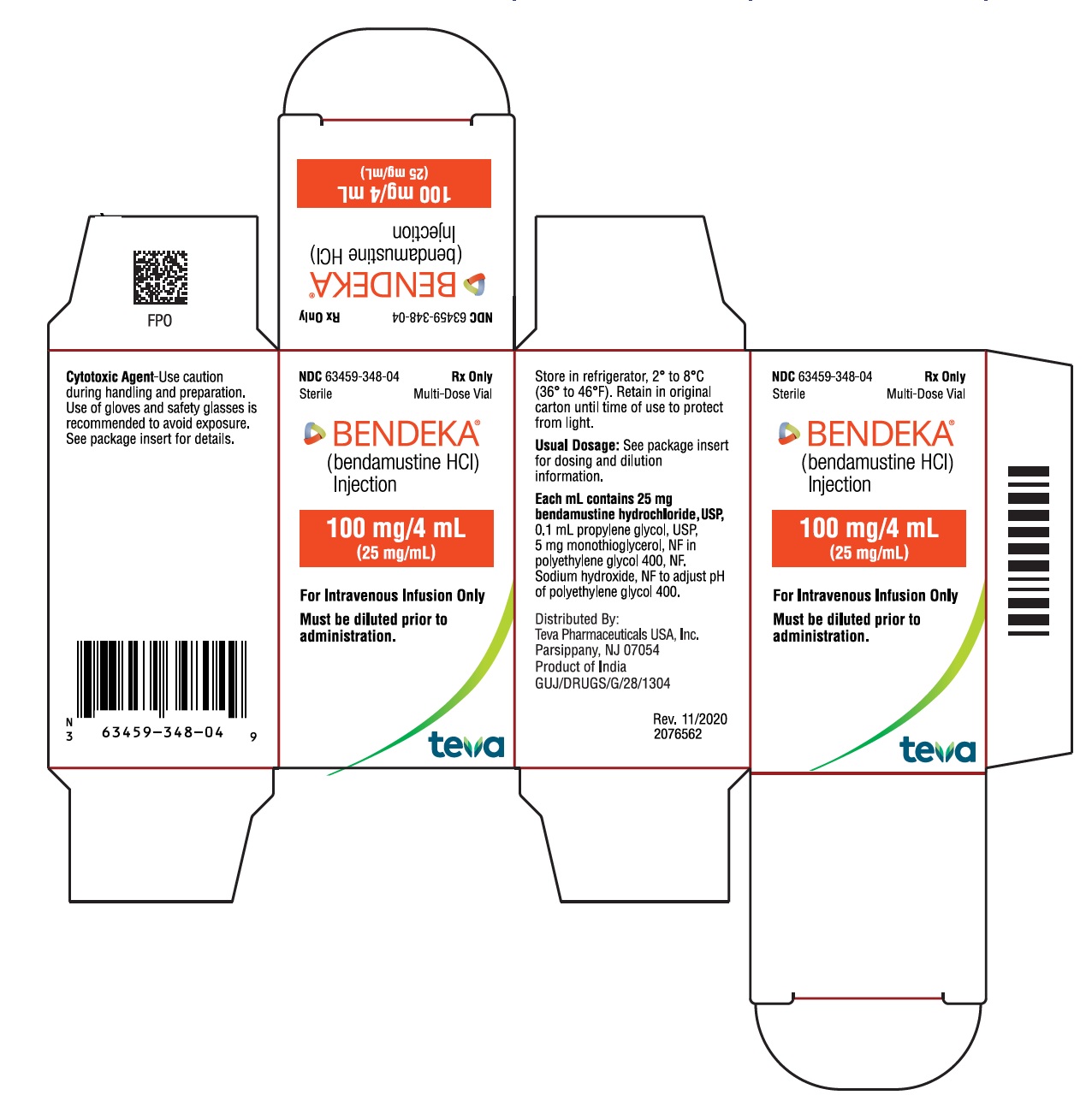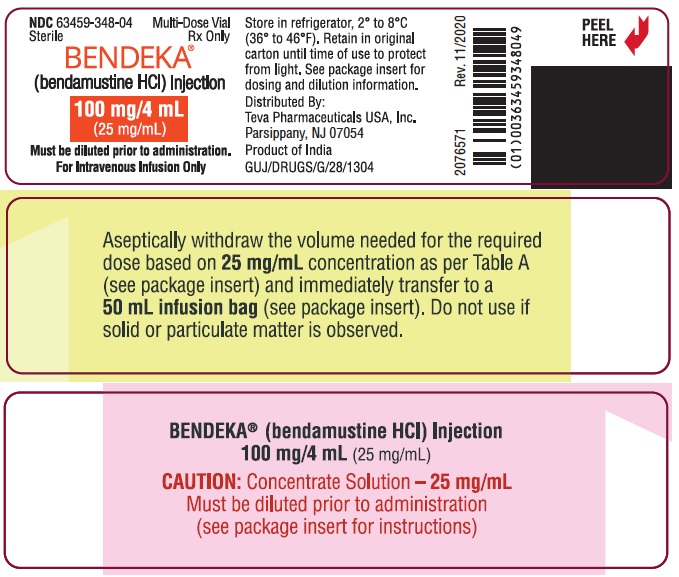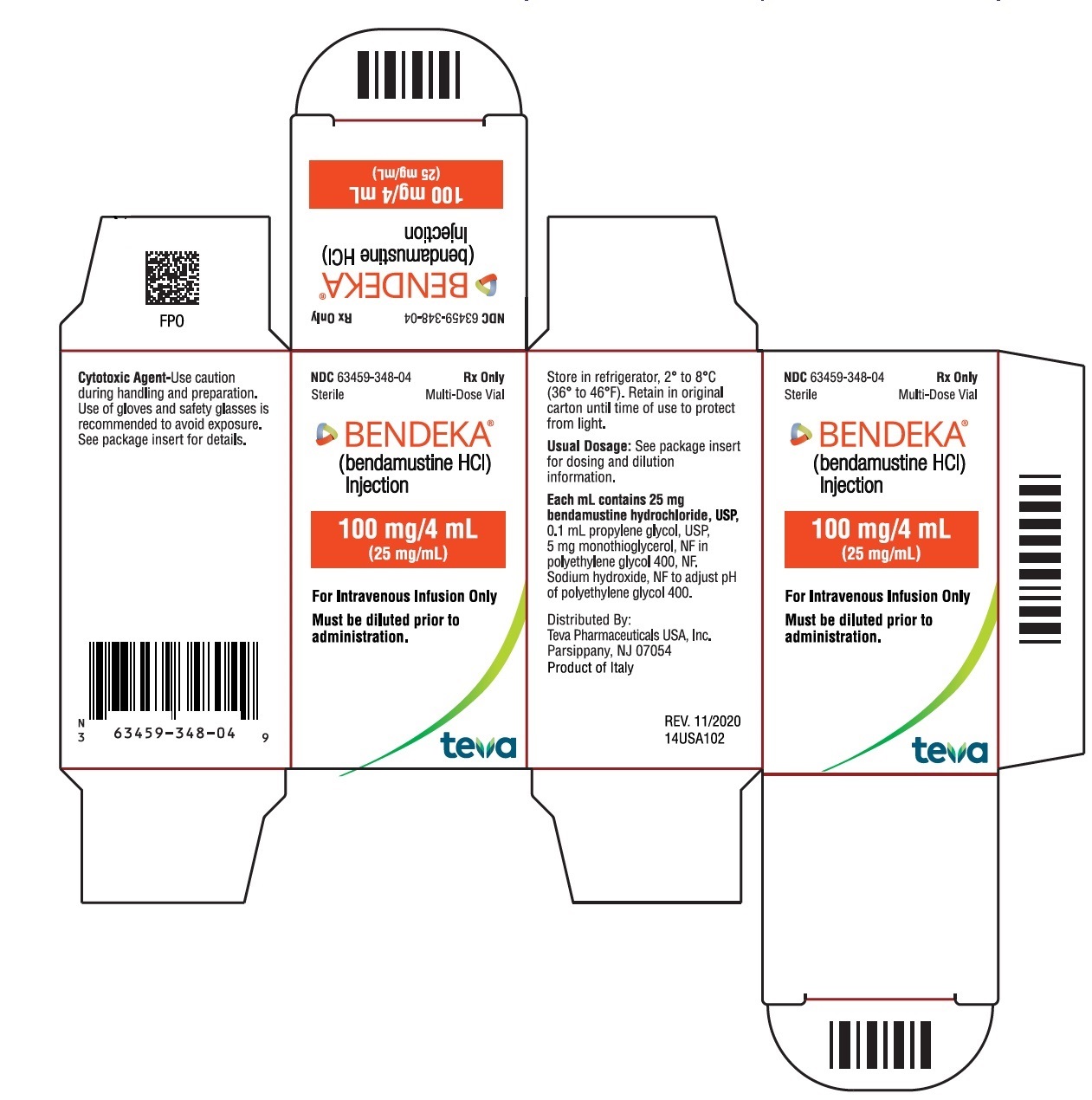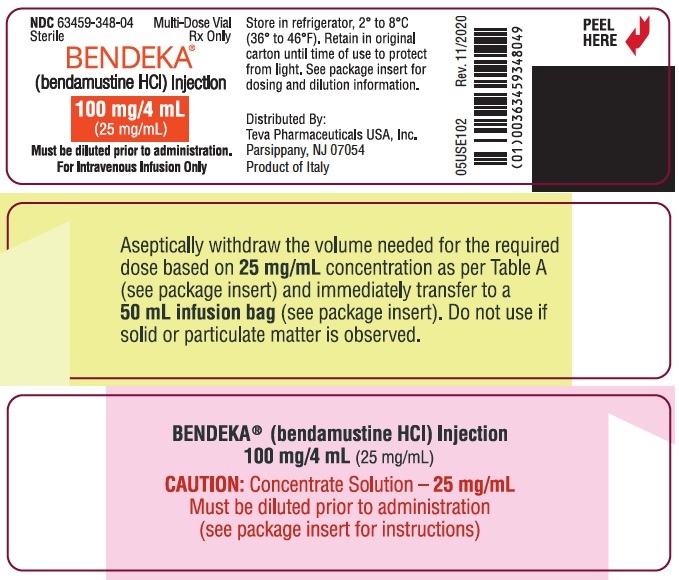 DRUG LABEL: Bendeka
NDC: 63459-348 | Form: INJECTION, SOLUTION
Manufacturer: Teva Pharmaceuticals USA, Inc.
Category: prescription | Type: HUMAN PRESCRIPTION DRUG LABEL
Date: 20240119

ACTIVE INGREDIENTS: BENDAMUSTINE HYDROCHLORIDE 25 mg/1 mL
INACTIVE INGREDIENTS: PROPYLENE GLYCOL; MONOTHIOGLYCEROL; POLYETHYLENE GLYCOL 400; SODIUM HYDROXIDE

HIGHLIGHTS OF PRESCRIBING INFORMATION

These highlights do not include all the information needed to use BENDEKA safely and effectively. See full prescribing information for BENDEKA.
BENDEKA® (bendamustine hydrochloride injection), for intravenous use
Initial U.S. Approval: 2008

1 INDICATIONS AND USAGE

BENDEKA injection is an alkylating drug indicated for treatment of patients with:

- Chronic lymphocytic leukemia (CLL). Efficacy relative to first line therapies other than chlorambucil has not been established. (1.1)
- Indolent B-cell non-Hodgkin lymphoma (NHL) that has progressed during or within six months of treatment with rituximab or a rituximab-containing regimen. (1.2)

2 DOSAGE AND ADMINISTRATION

For CLL:

- 100 mg/m^2 infused intravenously over 10 minutes on Days 1 and 2 of a 28-day cycle, up to 6 cycles. (2.1)

For NHL:

- 120 mg/m^2 infused intravenously over 10 minutes on Days 1 and 2 of a 21-day cycle, up to 8 cycles. (2.2)

3 DOSAGE FORMS AND STRENGTHS

Injection: 100 mg/4 mL (25 mg/mL) in a multiple-dose vial. (3)

4 CONTRAINDICATIONS

BENDEKA is contraindicated in patients with a history of a hypersensitivity reaction to bendamustine, polyethylene glycol 400, propylene glycol, or monothioglycerol. Reactions to bendamustine hydrochloride have included anaphylaxis and anaphylactoid reactions (4, 5.4)

5 WARNINGS AND PRECAUTIONS

- Myelosuppression: Delay or reduce dose, and restart treatment based on ANC and platelet count recovery. (2.1, 5.1)
- Infections: Monitor for fever and other signs of infection or reactivation of infections and treat promptly. (5.2)
- Progressive multifocal leukoencephalopathy (PML): Monitor for new or worsening neurological, cognitive or behavioral signs or symptoms suggestive of PML. (5.3)
- Anaphylaxis and Infusion Reactions: Severe anaphylactic reactions have occurred. Monitor clinically and discontinue drug for severe reactions. Pre-medicate in subsequent cycles for milder reactions. (5.4)
- Tumor Lysis Syndrome: May lead to acute renal failure and death; anticipate and use supportive measures in patients at high risk. (5.5)
- Skin Reactions: Discontinue for severe skin reactions. Cases of SJS, DRESS and TEN, some fatal, have been reported. (5.6).
- Hepatotoxicity: Monitor liver chemistry tests prior to and during treatment. (5.7)
- Other Malignancies: Pre-malignant and malignant diseases have been reported. (5.8)
- Extravasation Injury: Take precautions to avoid extravasation, including monitoring intravenous infusion site during and after administration. (5.9)
- Embryo-Fetal Toxicity: Can cause fetal harm. Advise females of reproductive potential and males with female partners of reproductive potential of the potential risk to a fetus and to use an effective method of contraception. (5.10, 8.1, 8.3)

6 ADVERSE REACTIONS

- Adverse reactions (frequency >5%) during infusion and within 24 hours post-infusion are nausea and fatigue. (6.1)
- Most common adverse reactions (≥15%) for CLL are anemia, thrombocytopenia, neutropenia, lymphopenia, leukopenia, hyperbilirubinemia, pyrexia, nausea, vomiting. (6.1, 6.2)
- Most common adverse reactions (≥15%) for NHL are lymphopenia, leukopenia, anemia, neutropenia, thrombocytopenia, nausea, fatigue, vomiting, diarrhea, pyrexia, constipation, anorexia, cough, headache, weight decreased, dyspnea, rash, and stomatitis. (6.1)

To report SUSPECTED ADVERSE REACTIONS, contact Teva Pharmaceuticals at 1-888-483-8279 or FDA at 1-800-FDA-1088 or www.fda.gov/medwatch.

7 DRUG INTERACTIONS

Consider alternative therapies that are not CYP1A2 inducers or inhibitors during treatment with BENDEKA. (7.1)

8 USE IN SPECIFIC POPULATIONS

- Lactation: Advise not to breastfeed. (8.2)
- Infertility: May impair fertility. (8.3)
- Renal Impairment: Do not use in patients with creatinine clearance <30 mL/min. (8.6)
- Hepatic Impairment: Do not use in patients with total bilirubin 1.5-3 × ULN and AST or ALT 2.5-10 × ULN, or total bilirubin > 3 × ULN. (8.7)

FULL PRESCRIBING INFORMATION

1 INDICATIONS AND USAGE

1.1 Chronic Lymphocytic Leukemia (CLL)

BENDEKA® is indicated for the treatment of patients with chronic lymphocytic leukemia. Efficacy relative to first line therapies other than chlorambucil has not been established.

1.2 Non-Hodgkin Lymphoma (NHL)

BENDEKA is indicated for the treatment of patients with indolent B-cell non-Hodgkin lymphoma that has progressed during or within six months of treatment with rituximab or a rituximab-containing regimen.

2 DOSAGE AND ADMINISTRATION

2.1 Dosing Instructions for CLL

Recommended Dosage:
The recommended dosage is 100 mg/m^2 administered intravenously over 10 minutes on Days 1 and 2 of a 28-day cycle, up to 6 cycles.

Dose Delays, Dosage Modifications and Reinitiation of Therapy for CLL:
Delay BENDEKA administration in the event of Grade 4 hematologic toxicity or clinically significant greater than or equal to Grade 2 non-hematologic toxicity. Once non-hematologic toxicity has recovered to less than or equal to Grade 1 and/or the blood counts have improved [Absolute Neutrophil Count (ANC) greater than or equal to 1 x 10^9/L, platelets greater than or equal to 75 x 10^9/L], reinitiate BENDEKA (bendamustine hydrochloride) injection at the discretion of the treating physician. In addition, consider dose reduction. [see Warnings and Precautions (5.1)]

Dosage modifications for hematologic toxicity: for Grade 3 or greater toxicity, reduce the dose to 50 mg/m^2 on Days 1 and 2 of each cycle; if Grade 3 or greater toxicity recurs, reduce the dose to 25 mg/m^2 on Days 1 and 2 of each cycle.

Dosage modifications for non-hematologic toxicity: for clinically significant Grade 3 or greater toxicity, reduce the dose to 50 mg/m^2 on Days 1 and 2 of each cycle.

Consider dosage re-escalation in subsequent cycles at the discretion of the treating physician.

2.2 Dosing Instructions for NHL

Recommended Dosage:
The recommended dose is 120 mg/m^2 administered intravenously over 10 minutes on Days 1 and 2 of a 21-day cycle, up to 8 cycles.

Dose Delays, Dosage Modifications and Reinitiation of Therapy for NHL:
Delay BENDEKA administration in the event of a Grade 4 hematologic toxicity or clinically significant greater than or equal to Grade 2 non-hematologic toxicity. Once non-hematologic toxicity has recovered to less than or equal to Grade 1 and/or the blood counts have improved [Absolute Neutrophil Count (ANC) greater than or equal to 1 x 10^9/L, platelets greater than or equal to 75 x 10^9/L], reinitiate BENDEKA at the discretion of the treating physician. In addition, consider dose reduction. [see Warnings and Precautions (5.1)]

Dosage modifications for hematologic toxicity: for Grade 4 toxicity, reduce the dose to 90 mg/m^2 on Days 1 and 2 of each cycle; if Grade 4 toxicity recurs, reduce the dose to 60 mg/m^2 on Days 1 and 2 of each cycle.

Dosage modifications for non-hematologic toxicity: for Grade 3 or greater toxicity, reduce the dose to 90 mg/m^2 on Days 1 and 2 of each cycle; if Grade 3 or greater toxicity recurs, reduce the dose to 60 mg/m^2 on Days 1 and 2 of each cycle.

2.3 Preparation for Intravenous Administration

BENDEKA is a hazardous drug. Follow applicable special handling and disposal procedures.^1

BENDEKA is in a multiple-dose vial. At room temperature, BENDEKA is a clear, and colorless to yellow ready-to-dilute solution. Store BENDEKA at recommended refrigerated storage conditions (2°C to 8°C or 36°F to 46°F). When refrigerated, the contents may freeze. Allow the vial to reach room temperature (15°C to 30°C or 59°F to 86°F) prior to use. Do not use the product if particulate matter is observed after achieving room temperature.

Intravenous Infusion

- Aseptically withdraw the volume needed for the required dose from the 25 mg/mL solution as per Table A below and immediately transfer the solution to a 50 mL infusion bag of one of the following diluents:
  - 0.9% Sodium Chloride Injection, USP; or
  - 2.5% Dextrose/0.45% Sodium Chloride Injection, USP; or
  - 5% Dextrose Injection, USP.

The resulting final concentration of bendamustine hydrochloride in the infusion bag should be within 0.49 mg/mL to 5.6 mg/mL. After transferring, thoroughly mix the contents of the infusion bag. The admixture should be a clear, and colorless to yellow solution.

No other diluents have been shown to be compatible. The 5% Dextrose Injection, USP, offers a sodium-free method of administration for patients with certain medical conditions requiring restricted sodium intake.

Table A: Volume (mL) of BENDEKA required for dilution into 50 mL of 0.9% saline, or 0.45% saline/2.5% dextrose or 5% dextrose for a given dose (mg/m^2) and Body Surface Area (m^2)
Body Surface Area (m^2) | Volume of BENDEKA to withdraw (mL)
Body Surface Area (m^2) | 120 mg/m^2 | 100 mg/m^2 | 90 mg/m^2 | 60 mg/m^2 | 50 mg/m^2 | 25 mg/m^2
1 | 4.8 | 4 | 3.6 | 2.4 | 2 | 1
1.1 | 5.3 | 4.4 | 4 | 2.6 | 2.2 | 1.1
1.2 | 5.8 | 4.8 | 4.3 | 2.9 | 2.4 | 1.2
1.3 | 6.2 | 5.2 | 4.7 | 3.1 | 2.6 | 1.3
1.4 | 6.7 | 5.6 | 5 | 3.4 | 2.8 | 1.4
1.5 | 7.2 | 6 | 5.4 | 3.6 | 3 | 1.5
1.6 | 7.7 | 6.4 | 5.8 | 3.8 | 3.2 | 1.6
1.7 | 8.2 | 6.8 | 6.1 | 4.1 | 3.4 | 1.7
1.8 | 8.6 | 7.2 | 6.5 | 4.3 | 3.6 | 1.8
1.9 | 9.1 | 7.6 | 6.8 | 4.6 | 3.8 | 1.9
2 | 9.6 | 8 | 7.2 | 4.8 | 4 | 2
2.1 | 10.1 | 8.4 | 7.6 | 5 | 4.2 | 2.1
2.2 | 10.6 | 8.8 | 7.9 | 5.3 | 4.4 | 2.2
2.3 | 11 | 9.2 | 8.3 | 5.5 | 4.6 | 2.3
2.4 | 11.5 | 9.6 | 8.6 | 5.8 | 4.8 | 2.4
2.5 | 12 | 10 | 9 | 6 | 5 | 2.5
2.6 | 12.5 | 10.4 | 9.4 | 6.2 | 5.2 | 2.6
2.7 | 13 | 10.8 | 9.7 | 6.5 | 5.4 | 2.7
2.8 | 13.4 | 11.2 | 10.1 | 6.7 | 5.6 | 2.8
2.9 | 13.9 | 11.6 | 10.4 | 7 | 5.8 | 2.9
3 | 14.4 | 12 | 10.8 | 7.2 | 6 | 3

Parenteral drug products should be inspected visually for particulate matter and discoloration prior to administration whenever solution and container permit. Any unused solution should be discarded according to institutional procedures for antineoplastics.

2.4 Admixture Stability

BENDEKA contains no antimicrobial preservative. Prepare the admixture as close as possible to the time of patient administration.

If diluted with 0.9% Sodium Chloride Injection, USP, or 2.5% Dextrose/0.45% Sodium Chloride Injection, USP, the final admixture is stable for 24 hours when stored refrigerated (2°C to 8°C or 36°F to 46°F) or for 6 hours when stored at room temperature (15°C to 30°C or 59°F to 86°F) and room light. Administration of diluted BENDEKA (bendamustine hydrochloride) injection must be completed within this period of time.

In the event that 5% Dextrose Injection, USP is utilized, the final admixture is stable for 24 hours when stored refrigerated (2°C to 8°C or 36°F to 46°F) or for only 3 hours when stored at room temperature (15°C to 30°C or 59°F to 86°F) and room light. Administration of diluted BENDEKA must be completed within this period of time.

Retain the partially used vial in original package to protect from light and store refrigerated (2°C to 8°C or 36°F to 46°F) if additional dose withdrawal from the same vial is intended.

2.5 Stability of Partially Used Vials (Needle Punched Vials)

BENDEKA is supplied in a multiple-dose vial. Although it does not contain any antimicrobial preservative, BENDEKA is bacteriostatic. The partially used vials are stable for up to 28 days when stored in its original carton under refrigeration (2°C to 8°C or 36°C to 46°F). Each vial is not recommended for more than a total of six (6) dose withdrawals.

After first use, store the partially used vial in the refrigerator in the original carton at 2°C to 8°C or 36°F to 46°F and then discard after 28 days.

3 DOSAGE FORMS AND STRENGTHS

Injection: 100 mg/4 mL (25 mg/mL) as a clear and colorless to yellow ready-to-dilute solution in a multiple-dose vial.

4 CONTRAINDICATIONS

BENDEKA is contraindicated in patients with a known hypersensitivity (e.g., anaphylactic and anaphylactoid reactions) to bendamustine, polyethylene glycol 400, propylene glycol, or monothioglycerol. [see Warnings and Precautions (5.4)]

5 WARNINGS AND PRECAUTIONS

5.1 Myelosuppression

Bendamustine hydrochloride caused severe myelosuppression (Grade 3-4) in 98% of patients in the two NHL studies [see Adverse Reactions (6.1)]. Three patients (2%) died from myelosuppression-related adverse reactions; one each from neutropenic sepsis, diffuse alveolar hemorrhage with Grade 3 thrombocytopenia, and pneumonia from an opportunistic infection (CMV).

BENDEKA causes myelosuppression. Monitor complete blood counts, including leukocytes, platelets, hemoglobin (Hgb), and neutrophils frequently. In the clinical trials, blood counts were monitored every week initially. Hematologic nadirs occurred predominantly in the third week of therapy. Myelosuppression may require dose delays and/or subsequent dose reductions if recovery to the recommended values has not occurred by the first day of the next scheduled cycle. Prior to the initiation of the next cycle of therapy, the ANC should be ≥ 1 x 10^9/L and the platelet count should be ≥ 75 x 10^9/L. [see Dosage and Administration (2.1)]

5.2 Infections

Infection, including pneumonia, sepsis, septic shock, hepatitis and death has occurred in adult and pediatric patients in clinical trials and in postmarketing reports for bendamustine hydrochloride [see Adverse Reactions (6.1, 6.2)]. Patients with myelosuppression following treatment with bendamustine hydrochloride are more susceptible to infections. Advise patients with myelosuppression following BENDEKA treatment to contact a physician immediately if they have symptoms or signs of infection.

Patients treated with BENDEKA are at risk for reactivation of infections including (but not limited to) hepatitis B, cytomegalovirus, Mycobacterium tuberculosis, and herpes zoster. Patients should undergo appropriate measures (including clinical and laboratory monitoring, prophylaxis, and treatment) for infection and infection reactivation prior to administration.

5.3 Progressive Multifocal Leukoencephalopathy (PML)

Progressive multifocal leukoencephalopathy (PML), including fatal cases, have occurred following treatment with bendamustine, primarily in combination with rituximab or obinutuzumab [see Adverse Reactions (6.2)]. Consider PML in the differential diagnosis in patients with new or worsening neurological, cognitive or behavioral signs or symptoms. If PML is suspected, withhold BENDEKA treatment and perform appropriate diagnostic evaluations. Consider discontinuation or reduction of any concomitant chemotherapy or immunosuppressive therapy in patients who develop PML.

5.4 Anaphylaxis and Infusion Reactions

Infusion reactions to bendamustine hydrochloride have occurred commonly in clinical trials [see Adverse Reactions (6.1)]. Symptoms include fever, chills, pruritus and rash. In rare instances, severe anaphylactic and anaphylactoid reactions have occurred, particularly in the second and subsequent cycles of therapy. Monitor clinically and discontinue drug for severe reactions. Ask patients about symptoms suggestive of infusion reactions after their first cycle of therapy. Patients who experienced Grade 3 or worse allergic-type reactions were not typically rechallenged. Consider measures to prevent severe reactions, including antihistamines, antipyretics and corticosteroids in subsequent cycles in patients who have experienced Grade 1 or 2 infusion reactions. Discontinue BENDEKA for patients with Grade 4 infusion reactions. Consider discontinuation for Grade 3 infusion reactions as clinically appropriate considering individual benefits, risks, and supportive care.

5.5 Tumor Lysis Syndrome

Tumor lysis syndrome associated with bendamustine hydrochloride has occurred in patients in clinical trials and in postmarketing reports [see Adverse Reactions (6.1)]. The onset tends to be within the first treatment cycle of bendamustine hydrochloride and, without intervention, may lead to acute renal failure and death. Preventive measures include vigorous hydration and close monitoring of blood chemistry, particularly potassium and uric acid levels. Allopurinol has also been used during the beginning of bendamustine hydrochloride therapy. However, there may be an increased risk of severe skin toxicity when bendamustine hydrochloride and allopurinol are administered concomitantly. [see Warnings and Precautions (5.6)]

5.6 Skin Reactions

Fatal and serious skin reactions have been reported with bendamustine hydrochloride injection treatment in clinical trials and postmarketing safety reports, including toxic skin reactions [Stevens-Johnson Syndrome (SJS), toxic epidermal necrolysis (TEN), and drug reaction with eosinophilia and systemic symptoms (DRESS)], bullous exanthema, and rash [see Adverse Reactions (6.1 and 6.2)]. Events occurred when bendamustine hydrochloride injection was given as a single agent and in combination with other anticancer agents or allopurinol.

Where skin reactions occur, they may be progressive and increase in severity with further treatment. Monitor patients with skin reactions closely. If skin reactions are severe or progressive, withhold or discontinue BENDEKA.

5.7 Hepatotoxicity

Fatal and serious cases of liver injury have been reported with bendamustine hydrochloride injection [see Adverse Reactions (6.1)]. Combination therapy, progressive disease or reactivation of hepatitis B were confounding factors in some patients [see Warnings and Precautions (5.2)]. Most cases were reported within the first three months of starting therapy. Monitor liver chemistry tests prior to and during BENDEKA therapy.

5.8 Other Malignancies

There are reports of pre-malignant and malignant diseases that have developed in patients who have been treated with bendamustine hydrochloride, including myelodysplastic syndrome, myeloproliferative disorders, acute myeloid leukemia, bronchial carcinoma, and non-melanoma skin cancer, including basal cell carcinoma and squamous cell carcinoma [see Adverse Reactions (6.2)].

Monitor patients for the development of secondary malignancies. Perform dermatologic evaluations during and after treatment with BENDEKA.

5.9 Extravasation Injury

Bendamustine hydrochloride extravasations have been reported in postmarketing resulting in hospitalizations from erythema, marked swelling, and pain [see Adverse Reactions (6.2)]. Assure good venous access prior to starting drug infusion and monitor the intravenous infusion site for redness, swelling, pain, infection, and necrosis during and after administration of BENDEKA.

5.10 Embryo-Fetal Toxicity

Based on findings from animal reproduction studies and the drug’s mechanism of action, BENDEKA can cause fetal harm when administered to a pregnant woman. Single intraperitoneal doses of bendamustine (that approximated the maximum recommended human dose based on body surface area) to pregnant mice and rats during organogenesis caused adverse developmental outcomes, including an increase in resorptions, skeletal and visceral malformations, and decreased fetal body weights. Advise pregnant women of the potential risk to a fetus. Advise females of reproductive potential to use an effective method of contraception during treatment with BENDEKA and for 6 months after the last dose. Advise males with female partners of reproductive potential to use effective contraception during treatment with BENDEKA and for 3 months after the last dose. [see (Use in Specific Populations 8.1, 8.3) and Clinical Pharmacology (12.1)]

6 ADVERSE REACTIONS

The following clinically significant adverse reactions have been associated with bendamustine hydrochloride in clinical trials and are discussed in greater detail in other sections of the prescribing information.

- Myelosuppression [see Warnings and Precautions (5.1)]
- Infections [see Warnings and Precautions (5.2)]
- Progressive Multifocal Leukoencephalopathy [see Warnings and Precautions (5.3)]
- Anaphylaxis and Infusion Reactions[see Warnings and Precautions (5.4)]
- Tumor Lysis Syndrome [see Warnings and Precautions (5.5)]
- Skin Reactions [see Warnings and Precautions (5.6)]
- Hepatotoxicity [see Warnings and Precautions (5.7)]
- Other Malignancies [see Warnings and Precautions (5.8)]
- Extravasation Injury [see Warnings and Precautions (5.9)]

6.1 Clinical Trials Experience

Because clinical trials are conducted under widely varying conditions, adverse reaction rates observed in the clinical trials of a drug cannot be directly compared to rates in the clinical trials of another drug and may not reflect the rates observed in practice.

The data described below reflect exposure to bendamustine hydrochloride in 329 patients who participated in an actively controlled trial (N=153) for the treatment of CLL and two single arm studies (N=176) for the treatment of indolent B cell NHL. Because clinical trials are conducted under widely varying conditions, adverse reaction rates observed in the clinical trials of a drug cannot be directly compared to rates in the clinical trials of another drug and may not reflect the rates observed in practice.

The safety of BENDEKA administered IV as a 50 mL admixture over a 10-minute infusion is supported by clinical trials using bendamustine hydrochloride administered IV as a 500 mL admixture over 30-60 minutes infusion time, as well as an open-label, crossover study in 81 ‘end-of-life’ cancer patients treated with BENDEKA. In total, safety data from clinical studies are available from over 400 cancer patients exposed to bendamustine hydrochloride at doses in the range used in the treatment of CLL and NHL.

No clinically significant differences in the adverse reaction profile were noted among bendamustine hydrochloride administered as a 500 mL admixture over standard infusion time (30-60 minutes) and BENDEKA administered as a 50 mL admixture in a ‘short-time’ infusion over 10 minutes.

The safety and tolerability of BENDEKA was evaluated in an 8-week clinical study of BENDEKA in 81 ‘end-of-life’ cancer patients, diagnosed with solid tumors and hematologic malignancies (excluding CLL). The population was 40-82 years of age, 58% females, 84% white, 12.3% Black, 1.2% Asian and 2.5% were classified as ‘other’. BENDEKA was administered IV at a 120 mg/m^2 dose as a 50 mL admixture over 10 minutes. Patients in the study received BENDEKA (50 mL IV, over 10 minutes) or bendamustine hydrochloride (500 mL IV, over 60 minutes) on Days 1 and 2 every 28 days for two consecutive 2-day cycles.

Adverse reactions (any grade) that occurred with a frequency greater than 5% during BENDEKA infusion and within one hour post-infusion were nausea (8.2%) and fatigue (5.5%).

Adverse reactions (any grade) that occurred with a frequency greater than 5% within 24 hours of BENDEKA were nausea (10.9%) and fatigue (8.2%).

Adverse reactions leading to study withdrawal in 4 patients receiving BENDEKA were pyrexia (1.2%), nausea (1.2%), vomiting (1.2%), pneumonia (1.2%) and fatigue (1.2%).

Chronic Lymphocytic Leukemia (CLL)
The data described below reflect exposure to bendamustine hydrochloride in 153 patients. Bendamustine hydrochloride was studied in an active-controlled randomized trial. The population was 45-77 years of age, 63% male, 100% white, and had treatment naïve CLL. All patients started the study at a dose of 100 mg/m^2 intravenously over 30 minutes on Days 1 and 2 every 28 days.

Adverse reactions were reported according to NCI CTC v.2.0. In the randomized CLL clinical study, non-hematologic adverse reactions (any grade) in the bendamustine hydrochloride group that occurred with a frequency greater than 15% were pyrexia (24%), nausea (20%), and vomiting (16%).

Other adverse reactions seen frequently in one or more studies included asthenia, fatigue, malaise, and weakness; dry mouth; somnolence; cough; constipation; headache; mucosal inflammation and stomatitis.

Worsening hypertension was reported in 4 patients treated with bendamustine hydrochloride in the randomized CLL clinical study and in none treated with chlorambucil. Three of these 4 adverse reactions were described as a hypertensive crisis and were managed with oral medications and resolved.

The most frequent adverse reactions leading to study withdrawal for patients receiving bendamustine hydrochloride were hypersensitivity (2%) and pyrexia (1%).

Table 1 contains the treatment emergent adverse reactions, regardless of attribution, that were reported in ≥ 5% of patients in either treatment group in the randomized CLL clinical study.

Table 1: Non-Hematologic Adverse Reactions Occurring in Randomized CLL Clinical Study in at Least 5% of Patients
 | Number (%) of patients
 | Bendamustine Hydrochloride (N=153) |  | Chlorambucil (N=143)
Body System Adverse Reaction | All Grades | Grade 3/4 | All Grades | Grade 3/4
Total number of patients with at least 1 adverse reaction | 121 (79) | 52 (34) | 96 (67) | 25 (17)
Gastrointestinal disorders
Nausea | 31 (20) | 1 (<1) | 21 (15) | 1 (<1)
Vomiting | 24 (16) | 1 (<1) | 9 (6) | 0
Diarrhea | 14 (9) | 2 (1) | 5 (3) | 0
General disorders and administration site conditions
Pyrexia | 36 (24) | 6 (4) | 8 (6) | 2 (1)
Fatigue | 14 (9) | 2 (1) | 8 (6) | 0
Asthenia | 13 (8) | 0 | 6 (4) | 0
Chills | 9 (6) | 0 | 1 (<1) | 0
Immune system disorders
Hypersensitivity | 7 (5) | 2 (1) | 3 (2) | 0
Infections and infestations
Nasopharyngitis | 10 (7) | 0 | 12 (8) | 0
Infection | 9 (6) | 3 (2) | 1 (<1) | 1 (<1)
Herpes simplex | 5 (3) | 0 | 7 (5) | 0
Investigations
Weight decreased | 11 (7) | 0 | 5 (3) | 0
Metabolism and nutrition disorders
Hyperuricemia | 11 (7) | 3 (2) | 2 (1) | 0
Respiratory, thoracic and mediastinal disorders
Cough | 6 (4) | 1 (<1) | 7 (5) | 1 (<1)
Skin and subcutaneous tissue disorders
Rash | 12 (8) | 4 (3) | 7 (5) | 3 (2)
Pruritus | 8 (5) | 0 | 2 (1) | 0

The Grade 3 and 4 hematology laboratory test values by treatment group in the randomized CLL clinical study are described in Table 2. These findings confirm the myelosuppressive effects seen in patients treated with bendamustine hydrochloride. Red blood cell transfusions were administered to 20% of patients receiving bendamustine hydrochloride compared with 6% of patients receiving chlorambucil.

Table 2: Incidence of Hematology Laboratory Abnormalities in Patients Who Received bendamustine hydrochloride or Chlorambucil in the Randomized CLL Clinical Study
Laboratory Abnormality | Bendamustine Hydrochloride (N=150) |  | Chlorambucil (N=141)
Laboratory Abnormality | All Grades n (%) | Grade 3/4 n (%) | All Grades n (%) | Grade 3/4 n (%)
Hemoglobin Decreased | 134 (89) | 20 (13) | 115 (82) | 12 (9)
Platelets Decreased | 116 (77) | 16 (11) | 110 (78) | 14 (10)
Leukocytes Decreased | 92 (61) | 42 (28) | 26 (18) | 4 (3)
Lymphocytes Decreased | 102 (68) | 70 (47) | 27 (19) | 6 (4)
Neutrophils Decreased | 113 (75) | 65 (43) | 86 (61) | 30 (21)

In the randomized CLL trial, 34% of patients had bilirubin elevations, some without associated significant elevations in AST and ALT. Grade 3 or 4 increased bilirubin occurred in 3% of patients. Increases in AST and ALT of Grade 3 or 4 were limited to 1% and 3% of patients, respectively. Patients treated with bendamustine hydrochloride may also have changes in their creatinine levels. If abnormalities are detected, monitoring of these parameters should be continued to ensure that significant deterioration does not occur.

Non-Hodgkin’s Lymphoma (NHL)
The data described below reflect exposure to bendamustine hydrochloride in 176 patients with indolent B-cell NHL treated in two single-arm studies. The population was 31-84 years of age, 60% male, and 40% female. The race distribution was 89% White, 7% Black, 3% Hispanic, 1% other, and <1% Asian. These patients received bendamustine hydrochloride at a dose of 120 mg/m^2 intravenously on Days 1 and 2 for up to eight 21-day cycles.

The adverse reactions occurring in at least 5% of the NHL patients, regardless of severity, are shown in Table 3. The most common non-hematologic adverse reactions (≥30%) were nausea (75%), fatigue (57%), vomiting (40%), diarrhea (37%) and pyrexia (34%). The most common non-hematologic Grade 3 or 4 adverse reactions (≥5%) were fatigue (11%), febrile neutropenia (6%), and pneumonia, hypokalemia and dehydration, each reported in 5% of patients.

Table 3: Non-Hematologic Adverse Reactions Occurring in at Least 5% of NHL Patients Treated with bendamustine hydrochloride by System Organ Class and Preferred Term (N=176)
Body System | Number (%) of patients*
Adverse Reaction | All Grades | Grade 3/4
Total number of patients with at least 1 adverse reaction | 176 (100) | 94 (53)
Cardiac Disorders
Tachycardia | 13 (7) | 0
Gastrointestinal disorders
Nausea | 132 (75) | 7 (4)
Vomiting | 71 (40) | 5 (3)
Diarrhea | 65 (37) | 6 (3)
Constipation | 51 (29) | 1 (<1)
Stomatitis | 27 (15) | 1 (<1)
Abdominal pain | 22 (13) | 2 (1)
Dyspepsia | 20 (11) | 0
Gastroesophageal reflux disease | 18 (10) | 0
Dry mouth | 15 (9) | 1 (<1)
Abdominal pain upper | 8 (5) | 0
Abdominal distension | 8 (5) | 0
General disorders and administration site conditions
Fatigue | 101 (57) | 19 (11)
Pyrexia | 59 (34) | 3 (2)
Chills | 24 (14) | 0
Edema peripheral | 23 (13) | 1 (<1)
Asthenia | 19 (11) | 4 (2)
Chest pain | 11 (6) | 1 (<1)
Infusion site pain | 11 (6) | 0
Pain | 10 (6) | 0
Catheter site pain | 8 (5) | 0
Infections and infestations
Herpes zoster | 18 (10) | 5 (3)
Upper respiratory tract infection | 18 (10) | 0
Urinary tract infection | 17 (10) | 4 (2)
Sinusitis | 15 (9) | 0
Pneumonia | 14 (8) | 9 (5)
Febrile neutropenia | 11 (6) | 11 (6)
Oral candidiasis | 11 (6) | 2 (1)
Nasopharyngitis | 11 (6) | 0
Investigations
Weight decreased | 31 (18) | 3 (2)
Metabolism and nutrition disorders
Anorexia | 40 (23) | 3 (2)
Dehydration | 24 (14) | 8 (5)
Decreased appetite | 22 (13) | 1 (<1)
Hypokalemia | 15 (9) | 9 (5)
Musculoskeletal and connective tissue disorders
Back pain | 25 (14) | 5 (3)
Arthralgia | 11 (6) | 0
Pain in extremity | 8 (5) | 2 (1)
Bone pain | 8 (5) | 0
Nervous system disorders
Headache | 36 (21) | 0
Dizziness | 25 (14) | 0
Dysgeusia | 13 (7) | 0
Psychiatric disorder
Insomnia | 23 (13) | 0
Anxiety | 14 (8) | 1 (<1)
Depression | 10 (6) | 0
Respiratory, thoracic and mediastinal disorders
Cough | 38 (22) | 1 (<1)
Dyspnea | 28 (16) | 3 (2)
Pharyngolaryngeal pain | 14 (8) | 1 (<1)
Wheezing | 8 (5) | 0
Nasal congestion | 8 (5) | 0
Skin and subcutaneous tissue disorders
Rash | 28 (16) | 1 (<1)
Pruritus | 11 (6) | 0
Dry skin | 9 (5) | 0
Night sweats | 9 (5) | 0
Hyperhidrosis | 8 (5) | 0
Vascular disorders
Hypotension | 10 (6) | 2 (1)
*Patients may have reported more than 1 adverse reaction.
NOTE: Patients counted only once in each preferred term category and once in each system organ class category.

Hematologic toxicities, based on laboratory values and CTC grade, in NHL patients treated in both single arm studies combined are described in Table 4. Clinically important chemistry laboratory values that were new or worsened from baseline and occurred in >1% of patients at grade 3 or 4, in NHL patients treated in both single arm studies combined were hyperglycemia (3%), elevated creatinine (2%), hyponatremia (2%), and hypocalcemia (2%).

Table 4: Incidence of Hematology Laboratory Abnormalities in Patients Who Received bendamustine hydrochloride in the NHL Studies
Hematology Variable | Percent of Patients
Hematology Variable | All Grades | Grade 3/4
Lymphocytes Decreased | 99 | 94
Leukocytes Decreased | 94 | 56
Hemoglobin Decreased | 88 | 11
Neutrophils Decreased | 86 | 60
Platelets Decreased | 86 | 25

In both studies, serious adverse reactions, regardless of causality, were reported in 37% of patients receiving bendamustine hydrochloride. The most common serious adverse reactions occurring in ≥5% of patients were febrile neutropenia and pneumonia. Other important serious adverse reactions reported in clinical trials and/or postmarketing experience were acute renal failure, cardiac failure, hypersensitivity, skin reactions, pulmonary fibrosis, and myelodysplastic syndrome.

Serious drug-related adverse reactions reported in clinical trials included myelosuppression, infection, pneumonia, tumor lysis syndrome and infusion reactions. Adverse reactions occurring less frequently but possibly related to bendamustine hydrochloride treatment were hemolysis, dysgeusia/taste disorder, atypical pneumonia, sepsis, herpes zoster, erythema, dermatitis, and skin necrosis.

6.2 Postmarketing Experience

The following adverse reactions have been identified during post-approval use of bendamustine hydrochloride. Because these reactions are reported voluntarily from a population of uncertain size, it is not always possible to reliably estimate their frequency or establish a causal relationship to drug exposure.

Blood and lymphatic systems disorders: Pancytopenia.

Cardiovascular disorders: Atrial fibrillation, congestive heart failure (some fatal), myocardial infarction (some fatal), palpitation.

General disorders and administration site conditions: Injection site reactions (including phlebitis, pruritus, irritation, pain, swelling), infusion site reactions (including phlebitis, pruritus, irritation, pain, swelling).

Immune system disorders: Anaphylaxis.

Infections and infestations: Pneumocystis jirovecii pneumonia, progressive multifocal leukoencephalopathy (PML).

Renal and urinary disorders: Nephrogenic diabetes insipidus (NDI).

Respiratory, thoracic and mediastinal disorders: Pneumonitis.

Skin and subcutaneous tissue disorders: Drug reaction with eosinophilia and systemic symptoms (DRESS), non-melanoma skin cancer (NMSC), Stevens-Johnson syndrome (SJS), toxic epidermal necrolysis (TEN).

7 DRUG INTERACTIONS

7.1 Effect of Other Drugs on BENDEKA

CYP1A2 Inhibitors
The coadministration of BENDEKA with CYP1A2 inhibitors may increase bendamustine plasma concentrations and may result in increased incidence of adverse reactions with BENDEKA [see Clinical Pharmacology (12.3)]. Consider alternative therapies that are not CYP1A2 inhibitors during treatment with BENDEKA.

CYP1A2 Inducers
The coadministration of BENDEKA with CYP1A2 inducers may decrease bendamustine plasma concentrations and may result in decreased efficacy of BENDEKA [see Clinical Pharmacology (12.3)]. Consider alternative therapies that are not CYP1A2 inducers during treatment with BENDEKA.

8 USE IN SPECIFIC POPULATIONS

8.1 Pregnancy

Risk Summary
In animal reproduction studies, intraperitoneal administration of bendamustine to pregnant mice and rats during organogenesis at doses 0.6 to 1.8 times the maximum recommended human dose (MRHD) resulted in embryo-fetal and/or infant mortality, structural abnormalities, and alterations to growth (see Data). There are no available data on bendamustine hydrochloride use in pregnant women to evaluate for a drug-associated risk of major birth defects, miscarriage or adverse maternal or fetal outcomes. Advise pregnant women of the potential risk to a fetus.

The estimated background risk of major birth defects and miscarriage for the indicated population is unknown. All pregnancies have a background risk of birth defect, loss, or other adverse outcomes. In the U.S. general population, the estimated background risk of major birth defects and miscarriage in clinically recognized pregnancies is 2 to 4% and 15 to 20%, respectively.

Data

Animal Data
Bendamustine hydrochloride was intraperitoneally administered once to mice from 210 mg/m^2 (approximately 1.8 times the MRHD) during organogenesis and caused an increase in resorptions, skeletal and visceral malformations (exencephaly, cleft palates, accessory rib, and spinal deformities) and decreased fetal body weights. This dose did not appear to be maternally toxic and lower doses were not evaluated. Repeat intraperitoneal administration of bendamustine hydrochloride to mice on gestation days 7 to 11 resulted in an increase in resorptions from 75 mg/m2 (approximately 0.6 times the MRHD) and an increase in abnormalities from 112.5 mg/m^2 (approximately 0.9 times the MRHD), similar to those seen after a single intraperitoneal administration.

Bendamustine hydrochloride was intraperitoneally administered once to rats from 120 mg/m^2 (approximately the MRHD) on gestation days 4, 7, 9, 11, or 13 and caused embryo and fetal lethality as indicated by increased resorptions and a decrease in live fetuses. A significant increase in external (effect on tail, head, and herniation of external organs [exomphalos]) and internal (hydronephrosis and hydrocephalus) malformations were seen in dosed rats.

8.2 Lactation

Risk Summary
There are no data on the presence of bendamustine hydrochloride or its metabolites in either human or animal milk, the effects on the breastfed child, or the effects on milk production. Because of the potential for serious adverse reactions in the breastfed child, advise patients that breastfeeding is not recommended during treatment with BENDEKA, and for 1 week after the last dose.

8.3 Females and Males of Reproductive Potential

BENDEKA can cause embryo-fetal harm when administered to a pregnant woman [see Use in Specific Populations (8.1)].

Pregnancy Testing
Pregnancy testing is recommended for females of reproductive potential prior to initiation of BENDEKA [see Use in Specific Populations (8.1)].

Contraception

Females
Advise female patients of reproductive potential to use effective contraception during treatment with BENDEKA and for 6 months after the last dose.

Males
Based on genotoxicity findings, advise males with female partners of reproductive potential to use effective contraception during treatment with BENDEKA and for 3 months after the last dose [see Nonclinical Toxicology (13.1)].

Infertility

Males
Based on findings from clinical studies, BENDEKA may impair male fertility. Impaired spermatogenesis, azoospermia, and total germinal aplasia have been reported in male patients treated with alkylating agents, especially in combination with other drugs. In some instances, spermatogenesis may return in patients in remission, but this may occur only several years after intensive chemotherapy has been discontinued. Advise patients of the potential risk to their reproductive capacities.

Based on findings from animal studies, BENDEKA may impair male fertility due to an increase in morphologically abnormal spermatozoa. The long-term effects of BENDEKA on male fertility, including the reversibility of adverse effects, have not been studied [see Nonclinical Toxicology (13.1)].

8.4 Pediatric Use

Safety and effectiveness in pediatric patients have not been established.

Safety, pharmacokinetics and efficacy were assessed in a single open-label trial (NCT01088984) in patients aged 1 to 19 years with relapsed or refractory acute leukemia, including 27 patients with acute lymphocytic leukemia (ALL) and 16 patients with acute myeloid leukemia (AML). Bendamustine hydrochloride was administered as an intravenous infusion over 60 minutes on Days 1 and 2 of each 21-day cycle. There was no treatment response (CR+ CRp) in any patient. The safety profile in these patients was consistent with that seen in adults, and no new safety signals were identified.

The pharmacokinetics of bendamustine in 43 patients, aged 1 to 19 years (median age of 10 years) were within range of values previously observed in adults given the same dose based on body surface area.

8.5 Geriatric Use

No overall differences in safety were observed between patients ≥65 years of age and younger patients. Efficacy was lower in patients 65 and over with CLL receiving bendamustine hydrochloride based upon an overall response rate of 47% for patients 65 and over and 70% for younger patients. Progression free survival was also longer in younger patients with CLL receiving bendamustine (19 months vs. 12 months). No overall differences in efficacy in patients with non-Hodgkin Lymphoma were observed between geriatric patients and younger patients.

8.6 Renal Impairment

Do not use BENDEKA in patients with creatinine clearance (CLcr) < 30 mL/min [see Clinical Pharmacology (12.3)].

8.7 Hepatic Impairment

Do not use BENDEKA in patients with AST or ALT 2.5-10 × upper limit of normal (ULN) and total bilirubin 1.5-3 × ULN, or total bilirubin > 3 × ULN [see Clinical Pharmacology (12.3)].

10 OVERDOSAGE

The intravenous LD50 of bendamustine hydrochloride is 240 mg/m^2 in the mouse and rat. Toxicities included sedation, tremor, ataxia, convulsions and respiratory distress.

Across all clinical experience, the reported maximum single dose received was 280 mg/m^2. Three of four patients treated at this dose showed ECG changes considered dose-limiting at 7 and 21 days post-dosing. These changes included QT prolongation (one patient), sinus tachycardia (one patient), ST and T wave deviations (two patients) and left anterior fascicular block (one patient). Cardiac enzymes and ejection fractions remained normal in all patients.

No specific antidote for bendamustine hydrochloride overdose is known. Management of overdosage should include general supportive measures, including monitoring of hematologic parameters and ECGs.

11 DESCRIPTION

BENDEKA (bendamustine hydrochloride) injection is an alkylating agent. The chemical name of bendamustine hydrochloride is 1H-benzimidazole-2-butanoic acid, 5-[bis(2-chloroethyl)amino]-1 methyl-, monohydrochloride. Its empirical molecular formula is C16H21Cl2N3O2 · HCl, and the molecular weight is 394.7. Bendamustine hydrochloride contains a mechlorethamine group and a benzimidazole heterocyclic ring with a butyric acid substituent, and has the following structural formula:

BENDEKA (bendamustine hydrochloride) injection for intravenous use is supplied as a sterile, clear, and colorless to yellow ready-to-dilute solution in a multiple-dose clear glass vial. Each milliliter contains 25 mg of bendamustine hydrochloride, USP, 0.1 mL of Propylene Glycol, USP, 5 mg of Monothioglycerol, NF, in Polyethylene Glycol 400, NF. Sodium hydroxide may have been used to adjust the acidity of polyethylene glycol 400.

12 CLINICAL PHARMACOLOGY

12.1 Mechanism of Action

Bendamustine is a bifunctional mechlorethamine derivative containing a purine-like benzimidazole ring. Mechlorethamine and its derivatives form electrophilic alkyl groups. These groups form covalent bonds with electron-rich nucleophilic moieties, resulting in interstrand DNA crosslinks. The bifunctional covalent linkage can lead to cell death via several pathways. Bendamustine is active against both quiescent and dividing cells. The exact mechanism of action of bendamustine remains unknown.

12.2 Pharmacodynamics

Based on the pharmacokinetics/pharmacodynamics analyses of data from adult patients with NHL, nausea increased with increasing bendamustine Cmax.

Cardiac Electrophysiology
The effect of bendamustine on the QTc interval was evaluated in 53 patients with indolent NHL and mantle cell lymphoma on Day 1 of Cycle 1 after administration of rituximab at 375 mg/m^2 intravenous infusion followed by a 30-minute intravenous infusion of bendamustine at 90 mg/m^2/day. No mean changes greater than 20 milliseconds were detected up to one hour post infusion. The potential for delayed effects on the QT interval after one hour was not evaluated.

12.3 Pharmacokinetics

Following a single dose of 120 mg/m^2 of bendamustine hydrochloride over 10-minute infusion, the mean Cmax achieved was 35 µg/mL (range 6 to 49 µg/mL), occurring typically at the end of infusion. Little or no accumulation in plasma is expected for bendamustine administered on Days 1 and 2 of a 28-day cycle.

Distribution
The protein binding of bendamustine ranged from 94 to 96% and was concentration independent from 1 to 50 µg/mL. The blood to plasma concentration ratios in human blood ranged from 0.84 to 0.86 over a concentration range of 10 to 100 µg/mL.

The mean steady-state volume of distribution (VSS) of bendamustine was approximately 20 to 25 L.

Elimination
After a single intravenous dose of 120 mg/m^2 of bendamustine over 1 hour, the intermediate half-life (t½) of the parent compound is approximately 40 minutes. The mean terminal elimination t½ of two active metabolites, γ-hydroxybendamustine (M3) and N desmethylbendamustine (M4) are approximately 3 hours and 30 minutes, respectively. Bendamustine clearance in humans is approximately 700 mL/min.

Metabolism
Bendamustine is extensively metabolized via hydrolytic, oxidative, and conjugative pathways. Bendamustine is primarily metabolized via hydrolysis to monohydroxy (HP1) and dihydroxybendamustine (HP2) metabolites with low cytotoxic activity in vitro. Two active minor metabolites, M3 and M4, are primarily formed via CYP1A2 in vitro. M3 and M4 concentrations of these metabolites in plasma are 1/10th and 1/100th that of the parent compound, respectively.

Excretion
Following IV infusion of radiolabeled bendamustine hydrochloride in cancer patients, approximately 76% of the dose was recovered. Approximately 50% of the dose was recovered in the urine (3.3% unchanged) and approximately 25% of the dose was recovered in the feces. Less than 1% of the dose was recovered in the urine as M3 and M4, and less than 5% of the dose was recovered in the urine as HP2.

Specific Populations
No clinically meaningful effects on the pharmacokinetics of bendamustine were observed based on age (31 to 84 years), sex, mild to moderate renal impairment (CLcr ≥ 30 mL/min), or hepatic impairment with total bilirubin 1.5 < ULN and AST or ALT < 2.5 × ULN. The effects of severe renal impairment (CLcr < 30 mL/min), or hepatic impairment with total bilirubin 1.5-3 × ULN and AST or ALT 2.5-10 × ULN or total bilirubin > 3 × ULN on the pharmacokinetics of bendamustine is unknown.

Race/Ethnicity
Exposures in Japanese subjects (n=6) were 40% higher than that in non-Japanese subjects receiving the same dose. The clinical importance of this difference on the safety and efficacy of bendamustine hydrochloride in Japanese subjects has not been established.

Drug Interaction Studies

In Vitro Studies

Effect of Bendamustine on CYP Substrates
Bendamustine did not inhibit CYP1A2, 2C9/10, 2D6, 2E1, or 3A4/5. Bendamustine did not induce metabolism of CYP1A2, CYP2A6, CYP2B6, CYP2C8, CYP2C9, CYP2C19, CYP2E1, or CYP3A4/5.

Effect of Transporters on Bendamustine Hydrochloride
Bendamustine is a substrate of P-glycoprotein and breast cancer resistance protein (BCRP).

13 NONCLINICAL TOXICOLOGY

13.1 Carcinogenesis, Mutagenesis, Impairment of Fertility

Bendamustine was carcinogenic in mice. After intraperitoneal injections at 37.5 mg/m^2/day (the lowest dose tested, approximately 0.3 times the maximum recommended human dose [MRHD]) and 75 mg/m^2/day (approximately 0.6 times the MRHD) for 4 days, peritoneal sarcomas in female AB/Jena mice were produced. Oral administration at 187.5 mg/m^2/day (the only dose tested, approximately 1.6 times the MRHD) for 4 days induced mammary carcinomas and pulmonary adenomas.

Bendamustine is a mutagen and clastogen. In a bacterial reverse mutation assay (Ames assay), bendamustine was shown to increase revertant frequency in the absence and presence of metabolic activation. Bendamustine was clastogenic in human lymphocytes in vitro, and in rat bone marrow cells in vivo (increase in micronucleated polychromatic erythrocytes) from 37.5 mg/m^2, (the lowest dose tested, approximately 0.3 times the MRHD).

Bendamustine induced morphologic abnormalities in spermatozoa in mice. Following tail vein injection of bendamustine at 120 mg/m^2 or a saline control on days 1 and 2 for a total of 3 weeks, the number of spermatozoa with morphologic abnormalities was 16% higher in the bendamustine-treated group as compared to the saline control group.

14 CLINICAL STUDIES

14.1 Chronic Lymphocytic Leukemia (CLL)

The safety and efficacy of bendamustine hydrochloride were evaluated in an open-label, randomized, controlled multicenter trial comparing bendamustine hydrochloride to chlorambucil. The trial was conducted in 301 previously-untreated patients with Binet Stage B or C (Rai Stages I - IV) CLL requiring treatment. Need-to-treat criteria included hematopoietic insufficiency, B-symptoms, rapidly progressive disease or risk of complications from bulky lymphadenopathy. Patients with autoimmune hemolytic anemia or autoimmune thrombocytopenia, Richter’s syndrome, or transformation to prolymphocytic leukemia were excluded from the study.

The patient populations in the bendamustine hydrochloride and chlorambucil treatment groups were balanced with regard to the following baseline characteristics: age (median 63 vs. 66 years), gender (63% vs. 61% male), Binet stage (71% vs. 69% Binet B), lymphadenopathy (79% vs. 82%), enlarged spleen (76% vs. 80%), enlarged liver (48% vs. 46%), hypercellular bone marrow (79% vs. 73%), “B” symptoms (51% vs. 53%), lymphocyte count (mean 65.7x10^9/L vs. 65.1x10^9/L), and serum lactate dehydrogenase concentration (mean 370.2 vs. 388.4 U/L). Ninety percent of patients in both treatment groups had immuno-phenotypic confirmation of CLL (CD5, CD23 and either CD19 or CD20 or both).

Patients were randomly assigned to receive either bendamustine hydrochloride at 100 mg/m^2, administered intravenously over a period of 30 minutes on Days 1 and 2 or chlorambucil at 0.8 mg/kg (Broca’s normal weight) administered orally on Days 1 and 15 of each 28-day cycle. Efficacy endpoints of objective response rate and progression-free survival were calculated using a pre-specified algorithm based on NCI working group criteria for CLL.

The results of this open-label randomized study demonstrated a higher rate of overall response and a longer progression-free survival for bendamustine hydrochloride compared to chlorambucil (see Table 5). Survival data are not mature.

Table 5: Efficacy Data for CLL
 | Bendamustine Hydrochloride (N=153) | Chlorambucil (N=148) | p-value
Response Rate n (%)
Overall response rate | 90 (59) | 38 (26) | <0.0001
(95% CI) | (51, 66.6) | (18.6, 32.7)
Complete response (CR)* | 13 (8) | 1 (<1)
Nodular partial response (nPR)** | 4 (3) | 0
Partial response (PR) † | 73 (48) | 37 (25)
Progression-Free Survival††
Median, months (95% CI) | 18 (11.7, 23.5) | 6 (5.6, 8.6)
Hazard ratio (95% CI) | 0.27 (0.17, 0.43) |  | <0.0001
CI = confidence interval
* CR was defined as peripheral lymphocyte count ≤ 4 x 10^9/L, neutrophils ≥ 1.5 x 10^9/L, platelets >100 x 10^9/L, hemoglobin > 110g/L, without transfusions, absence of palpable hepatosplenomegaly, lymph nodes ≤ 1.5 cm, < 30% lymphocytes without nodularity in at least a normocellular bone marrow and absence of “B” symptoms. The clinical and laboratory criteria were required to be maintained for a period of at least 56 days.
** nPR was defined as described for CR with the exception that the bone marrow biopsy shows persistent nodules.
† PR was defined as ≥50% decrease in peripheral lymphocyte count from the pretreatment baseline value, and either ≥50% reduction in lymphadenopathy, or ≥50% reduction in the size of spleen or liver, as well as one of the following hematologic improvements: neutrophils ≥ 1.5 x 10^9/L or 50% improvement over baseline, platelets >100 x 10^9/L or 50% improvement over baseline, hemoglobin >110g/L or 50% improvement over baseline without transfusions, for a period of at least 56 days.
†† PFS was defined as time from randomization to progression or death from any cause.

Kaplan-Meier estimates of progression-free survival comparing bendamustine hydrochloride with chlorambucil are shown in Figure 1.

Figure 1. Progression-Free Survival

Progression – Free Survival (months)
Study Treatment | ____ Bendamustine Hydrochloride | _ _ _ Chlorambucil

14.2 Non-Hodgkin Lymphoma (NHL)

The efficacy of bendamustine hydrochloride was evaluated in a single arm study (NCT00139841) of 100 patients with indolent B-cell NHL that had progressed during or within six months of treatment with rituximab or a rituximab-containing regimen. Patients were included if they relapsed within 6 months of either the first dose (monotherapy) or last dose (maintenance regimen or combination therapy) of rituximab. All patients received bendamustine hydrochloride intravenously at a dose of 120 mg/m^2, on Days 1 and 2 of a 21-day treatment cycle. Patients were treated for up to 8 cycles.

The median age was 60 years, 65% were male, and 95% had a baseline WHO performance status of 0 or 1. Major tumor subtypes were follicular lymphoma (62%), diffuse small lymphocytic lymphoma (21%), and marginal zone lymphoma (16%). Ninety-nine percent of patients had received previous chemotherapy, 91% of patients had received previous alkylator therapy, and 97% of patients had relapsed within 6 months of either the first dose (monotherapy) or last dose (maintenance regimen or combination therapy) of rituximab.

Efficacy was based on the assessments by a blinded independent review committee (IRC) and included overall response rate (complete response + complete response unconfirmed + partial response) and duration of response (DR) as summarized in Table 6.

Table 6: Efficacy Data for NHL*
 | Bendamustine Hydrochloride (N=100)
Response Rate (%)
Overall response rate (CR+CRu+PR) | 74
(95% CI) | (64.3, 82.3)
Complete response (CR) | 13
Complete response unconfirmed (CRu) | 4
Partial response (PR) | 57
Duration of Response (DR)
Median, months (95% CI) | 9.2 months (7.1, 10.8)
CI = confidence interval
*IRC assessment was based on modified International Working Group response criteria (IWG-RC). Modifications to IWG-RC specified that a persistently positive bone marrow in patients who met all other criteria for CR would be scored as PR. Bone marrow sample lengths were not required to be ≥20 mm.

15 REFERENCES

1. OSHA Hazardous Drugs. OSHA. [http://www.osha.gov/SLTC/hazardousdrugs/index.html]

16 HOW SUPPLIED/STORAGE AND HANDLING

Safe Handling and Disposal
BENDEKA (bendamustine hydrochloride) injection is a hazardous drug. Follow applicable special handling and disposal procedures.^1 Care should be exercised in the handling and preparation of solutions prepared from BENDEKA (bendamustine hydrochloride) injection. The use of gloves and safety glasses is recommended to avoid exposure in case of breakage of the vial or other accidental spillage. If a solution of BENDEKA (bendamustine hydrochloride) injection contacts the skin, wash the skin immediately and thoroughly with soap and water. If BENDEKA (bendamustine hydrochloride) injection contacts the mucous membranes, flush thoroughly with water.

How Supplied
BENDEKA (bendamustine hydrochloride) injection is supplied in individual cartons of 5 mL clear multiple-dose vials containing 100 mg of bendamustine hydrochloride as a clear, and colorless to yellow ready-to-dilute solution.

- NDC 63459-348-04, 100 mg/4 mL (25 mg/mL)

Storage
Store BENDEKA (bendamustine hydrochloride) injection in refrigerator, 2°C to 8°C (36°F to 46°F). Retain in original carton until time of use to protect from light.

17 PATIENT COUNSELING INFORMATION

Myelosuppression
Inform patients of the likelihood that BENDEKA (bendamustine hydrochloride) injection will cause a decrease in white blood cells, platelets, and red blood cells. They will need frequent monitoring of these parameters. They should be instructed to report shortness of breath, significant fatigue, bleeding, fever, or other signs of infection [see Warnings and Precautions (5.1)].

Progressive Multifocal Leukoencephalopathy (PML)
Inform patients to immediately contact their healthcare provider if they experience confusion, memory loss, trouble thinking, difficulty talking or walking, vision loss or other neurological or cognitive symptoms [see Warnings and Precautions (5.3)].

Anaphylaxis and Infusion Reactions
Inform patients of the possibility of serious or mild allergic reactions and to immediately report rash, facial swelling, or difficulty breathing during or soon after infusion [see Warnings and Precautions (5.4)].

Skin Reactions
Advise patients that a mild rash or itching may occur during treatment with BENDEKA (bendamustine hydrochloride) injection. Advise patients to immediately report severe or worsening rash or itching [see Warnings and Precautions (5.6)].

Hepatotoxicity
Inform patients of the possibility of developing liver function abnormalities and serious hepatic toxicity. Advise patients to immediately contact their healthcare provider if signs of liver failure occur, including jaundice, anorexia, bleeding or bruising [see Warnings and Precautions (5.7)].

Fatigue
Advise patients that BENDEKA (bendamustine hydrochloride) injection may cause tiredness and to avoid driving any vehicle or operating any dangerous tools or machinery if they experience this side effect [see Adverse Reactions (6.1)].

Nausea and Vomiting
Advise patients that BENDEKA (bendamustine hydrochloride) injection may cause nausea and/or vomiting. Patients should report nausea and vomiting so that symptomatic treatment may be provided [see Adverse Reactions (6.1)].

Diarrhea
Advise patients that BENDEKA (bendamustine hydrochloride) injection may cause diarrhea. Patients should report diarrhea to the physician so that symptomatic treatment may be provided [see Adverse Reactions (6.1)].

Non-melanoma Skin Cancer (NMSC)
Advise patients to undergo regular skin cancer screenings, and to report any suspicious skin changes to their healthcare provider [see Warnings and Precautions (5.8)].

Embryo-Fetal Toxicity
Advise pregnant women and females of reproductive potential of the potential risk to a fetus. Advise females to inform their healthcare provider of a known or suspected pregnancy [see Warnings and Precautions (5.10), Use in Specific Populations (8.2, 8.3) and Nonclinical Toxicology (13.1)]. Advise female patients of reproductive potential to use effective contraception during treatment with BENDEKA and for 6 months after the last dose [see Use in Specific Populations (8.1, 8.3)]. Advise males with female partners of reproductive potential to use effective contraception during treatment with BENDEKA and for 3 months after the last dose [see Use in Specific Populations (8.3), and Nonclinical Toxicology (13.1)].

Lactation
Advise females not to breastfeed during treatment with BENDEKA and for 1 week after the last dose [see Use in Specific Populations (8.2)].

Infertility
Advise males of reproductive potential that BENDEKA may impair fertility [see Use in Specific Populations (8.3)].

BEN-012

Manufactured For:
Teva Pharmaceuticals
400 Interpace Parkway #3,
Parsippany, NJ 07054

All rights reserved.

PRINCIPAL DISPLAY PANEL - NDC: 63459-348-04 - Carton Label

NDC 63459-348-04
Sterile

Rx Only
Multi-Dose Vial

BENDEKA™
(bendamustine HCl) Injection

100 mg/4 mL
(25 mg/mL)

For Intravenous Infusion Only

Must be diluted prior to administration.

Distributed By:
Teva Pharmaceuticals USA, Inc.
North Wales, PA 19454
Product of India
GUJ/DRUGS/G/28/1304

PRINCIPAL DISPLAY PANEL - NDC: 63459-348-04 - Vial Label

NDC 63459-348-04
Sterile

Multi-Dose Vial
Rx Only

BENDEKA™
(bendamustine HCl) Injection

100 mg/4 mL
(25 mg/mL)

Must be diluted prior to administration.

For Intravenous Infusion Only

Store in refrigerator, 2° to 8°C (36° to 46 °F). Retain in original carton until time of use to protect from light. See package insert for dosing and dilution information.

Distributed By:
Teva Pharmaceuticals USA, Inc.
North Wales, PA 19454
Product of India
GUJ/DRUGS/G/28/1304

PRINCIPAL DISPLAY PANEL - NDC: 63459-348-04 - Alternate Carton Label

NDC 63459-348-04
Sterile

Rx Only
Multi-Dose Vial

BENDEKA™
(bendamustine HCl) Injection

100 mg/4 mL
(25 mg/mL)

For Intravenous Infusion Only

Must be diluted prior to administration.

Distributed By:
Teva Pharmaceuticals USA, Inc.
North Wales, PA 19454
Product of Italy

PRINCIPAL DISPLAY PANEL - NDC: 63459-348-04 - Alternate Vial Label

NDC 63459-348-04
Sterile

Multi-Dose Vial
Rx Only

BENDEKA™
(bendamustine HCl) Injection

100 mg/4 mL
(25 mg/mL)

Must be diluted prior to administration.

For Intravenous Infusion Only

Store in refrigerator, 2° to 8°C (36° to 46 °F). Retain in original carton until time of use to protect from light. See package insert for dosing and dilution information.

Distributed By:
Teva Pharmaceuticals USA, Inc.
North Wales, PA 19454
Product of Italy